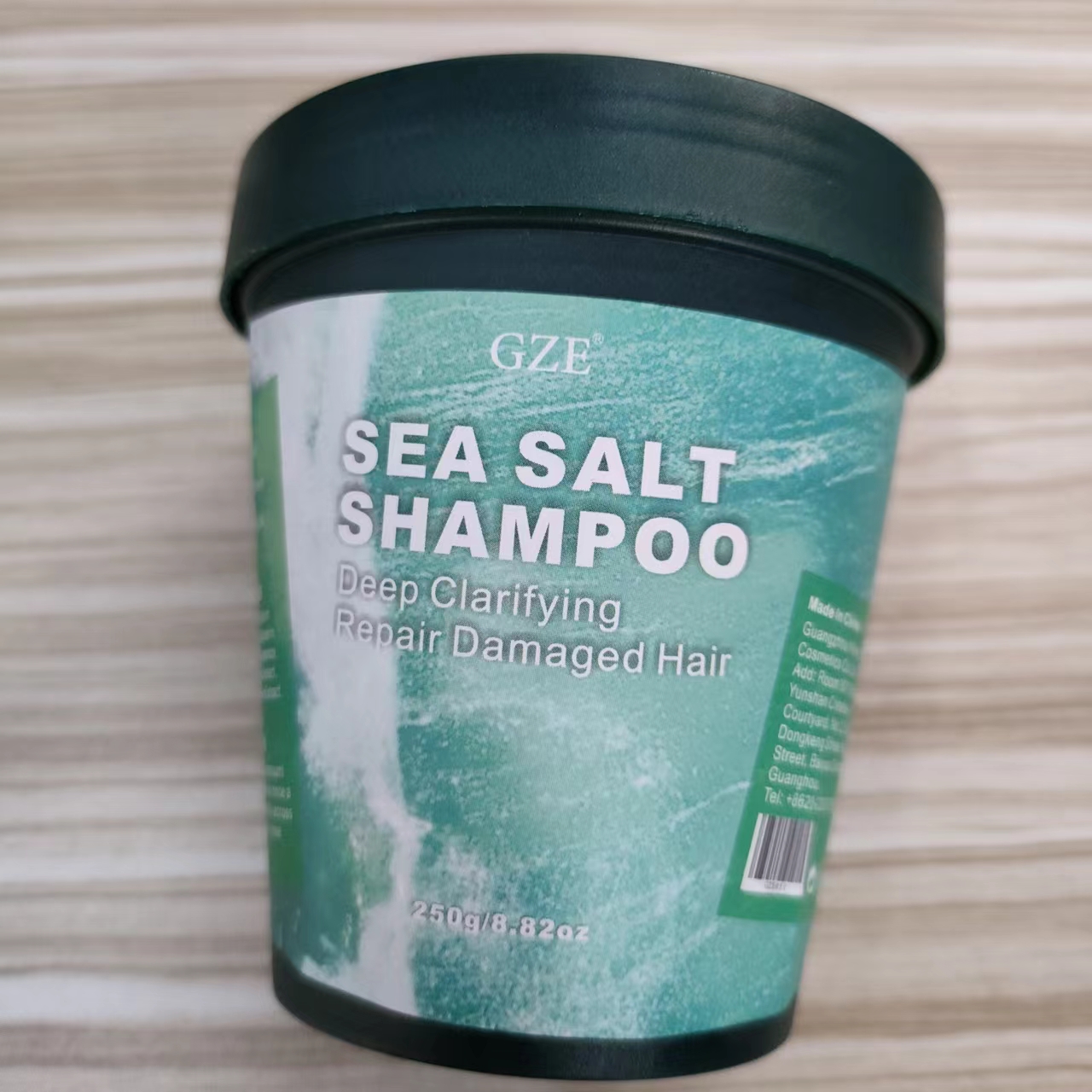 DRUG LABEL: GZE Sea SaltShampoo
NDC: 74458-051 | Form: GRANULE
Manufacturer: Guangzhou Yilong Cosmetics Co., Ltd
Category: otc | Type: HUMAN OTC DRUG LABEL
Date: 20241109

ACTIVE INGREDIENTS: CENTELLA ASIATICA TRITERPENOIDS 0.5 g/100 g; ZINGIBER OFFICINALE (GINGER) ROOT EXTRACT 0.5 g/100 g
INACTIVE INGREDIENTS: AQUA; SEA SALT; GLYCERIN; XANTHAN GUM; SODIUM LAURETH SULFATE

GZE SEA SALT SHAMPOO

ACTIVE INGREDIENT

Centella Asiatica Extract

Zingiber Officinale Extract

INACTIVE INGREDIENT

Sea Salt

Aqua

Sodium Laureth Sulfate

Glycerin

Xanthan Gum

Parfum

PURPOSE

Scalp cleansing.

INDICATIONS AND USAGE

Wet your hair, take an appropriate amount of sea salt shampoo and apply it to the scalp out, gently rub in a circular motion for about 2 minutes, and finally rinse with water until clean.

WARNINGS

For external use only.

Stop use and ask a doctor if rash occurs.

Do not use on damaged or broken skin.

When using this product keep out of eyes. Rinse with water to remove.

Keep out of reach of children. If swallowed, get medical help or contact a Poison Control Center right away.

DOSAGE AND ADMINISTRATION

Wet your hair, take an appropriate amount of sea salt shampoo and apply it to the scalp out, gently rub in a circular motion for about 2 minutes, and finally rinse with water until clean. Once every two weeks.